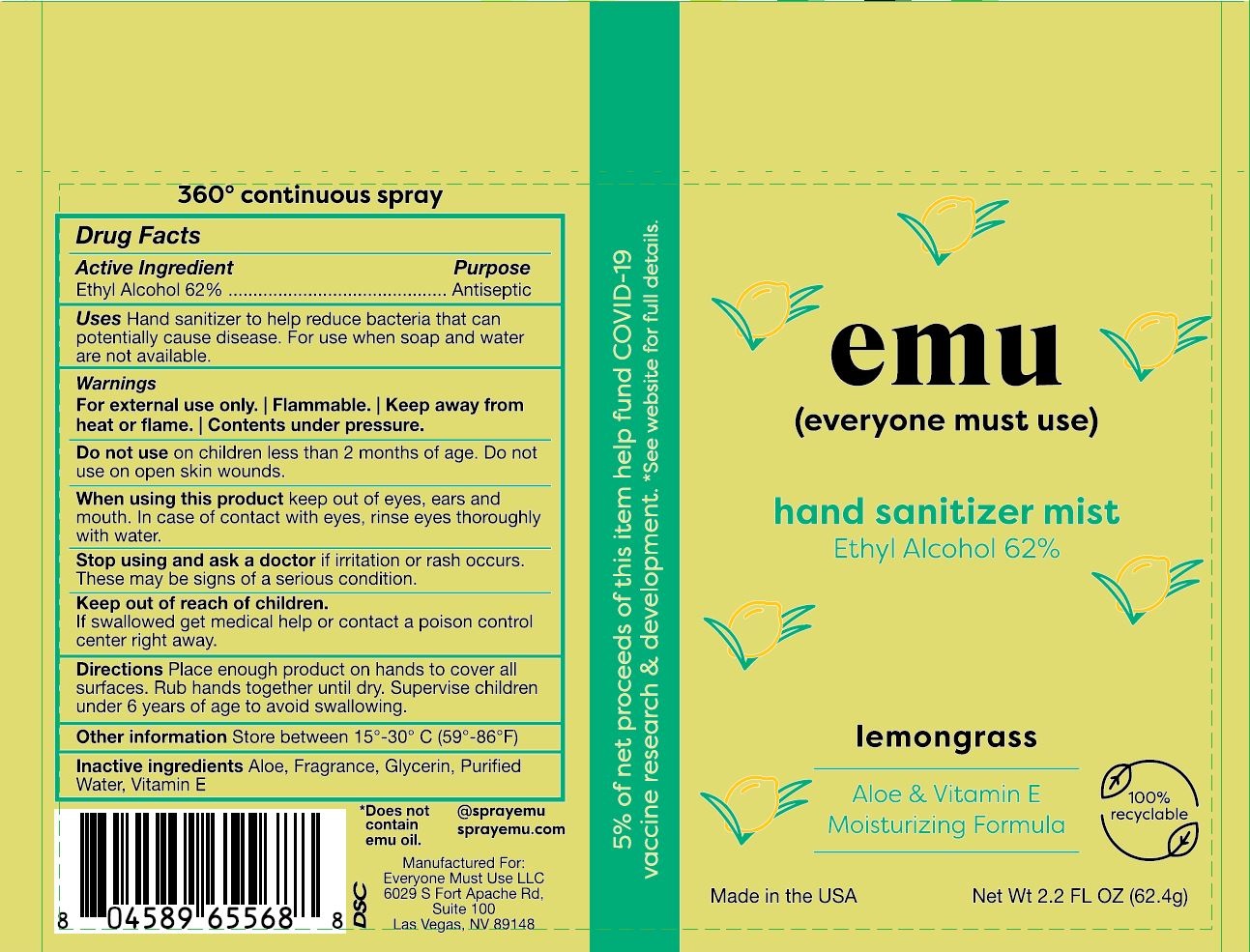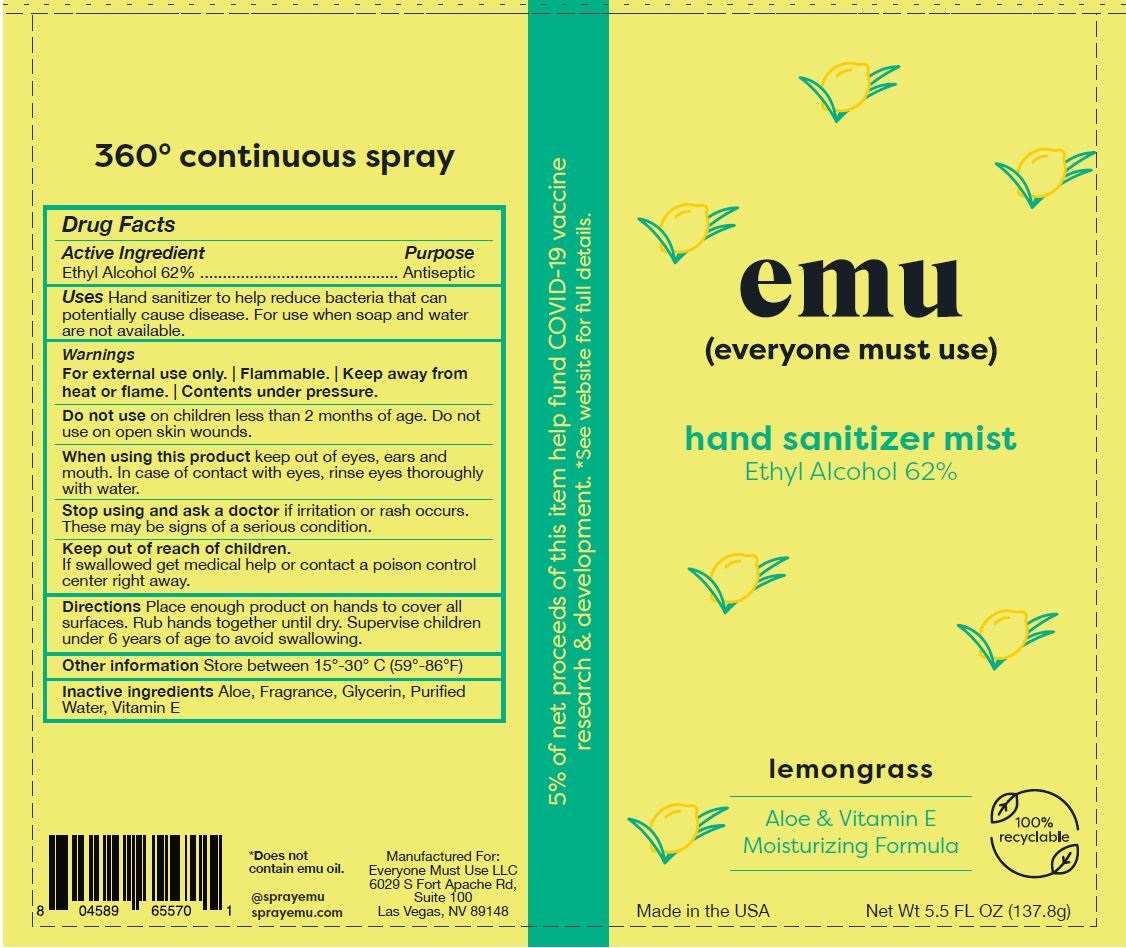 DRUG LABEL: Hand Sanitizer Mist Lemongrass
NDC: 80464-1001 | Form: SPRAY
Manufacturer: Everyone Must Use, LLC
Category: otc | Type: HUMAN OTC DRUG LABEL
Date: 20231221

ACTIVE INGREDIENTS: ALCOHOL 0.62 g/1 g
INACTIVE INGREDIENTS: GLYCERIN; ALOE; WATER; ALPHA-TOCOPHEROL ACETATE

EMU Everyone Must Use (Hand Sanitizer Ethyl Alcohol 62%) Lemongrass

Purpose

Antiseptic, Hand Sanitizer

Drug Facts

Active Ingredient | Purpose
Ethyl Alcohol 62% | Antiseptic

Uses

Hand Sanitizer to help reduce bacteria that potentially can cause disease. For use when soap and water are not available.

Warnings

For external use only. | Flammable.| Keep away from heat or flame. | Contents under pressure.

Do not use on children less than 2 months of age. Do not use on open skin wounds.

When using this product keep out of eyes, ears and mouth. In case of contact with eyes, rinse eyes thoroughly with water.

STOP USE

Stop using and ask a doctor if irritation or rash occurs. These may be signs of a serious condition.

Keep out of reach of children. If swallowed, get medical help or contact a Poison Control Center right away.

Directions

Place enough product on hands to cover all surfaces. Rub hands together until dry. Supervise children under 6 years of age to avoid swallowing.

Other information

Store between 15°-30° C (59°-86° F)

Inactive ingredients

Aloe, Fragrance, Glycerin, Purified Water, Vitamin E

QUESTIONS

@sprayemu

sprayemu.com

Package Label - Principal Display Panel

2.2 FL OZ NDC 80464-1001-1

Package Label - Principal Display Panel

5.5 FL OZ NDC 80464-1001-2